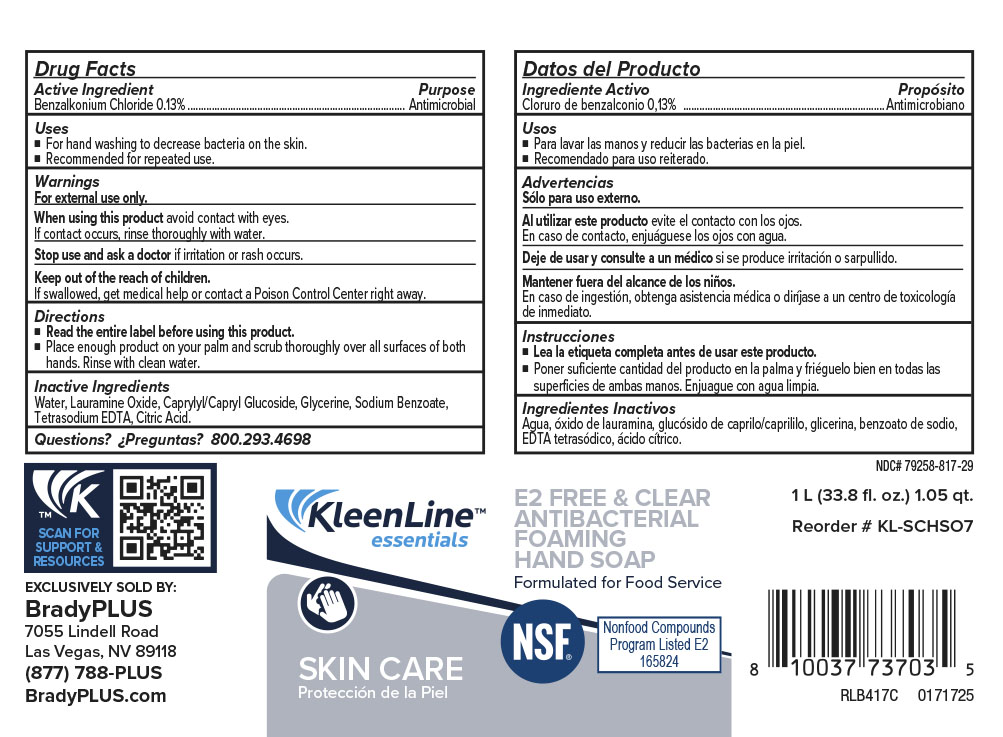 DRUG LABEL: KleenLine Essentials E2 Free and Clear Antibacterial HandSoap
NDC: 79258-817 | Form: LIQUID
Manufacturer: Brady Industries
Category: otc | Type: HUMAN OTC DRUG LABEL
Date: 20241216

ACTIVE INGREDIENTS: BENZALKONIUM CHLORIDE 0.13 mg/1 mL
INACTIVE INGREDIENTS: ANHYDROUS CITRIC ACID; TETRASODIUM EDTA; ALCOHOL; WATER; LAURTRIMONIUM CHLORIDE; SODIUM BENZOATE; GLYCERIN; CAPRYLYL/CAPRYL GLUCOSIDE

KleenLine Essentials Free & Clear Antibacterial Hand Soap

instructions

Read entire label before using this product

Place enough product on your palm and scrub thoroughly over all surfaces of both hands. Rinse with clean water.

keep our of reach

Keep out of reach of children

If swallowed get medical help or contact Poison Control Center right away.

inactives

Water, Lauramine Oxide, Caprylyl/Capryl Glucoside, Glycerin, Sodium Benzoate, Tetrasodium EDTA, Citric Acid

warnings

For esternal use only

When using this product avoid contact with eyes

If contact occurs, rinse thoroughly with water

Stop using and ask doctor if irritaition or rash occurs

purpose

Antimicrobial

usage

For hand washing to reduce acteria on ski

recommended for repeated use

DOSAGE AND ADMINISTRATION

Place enough product on palm and scrub thoroughly over all surfaces of both hands. Rinse with clean water